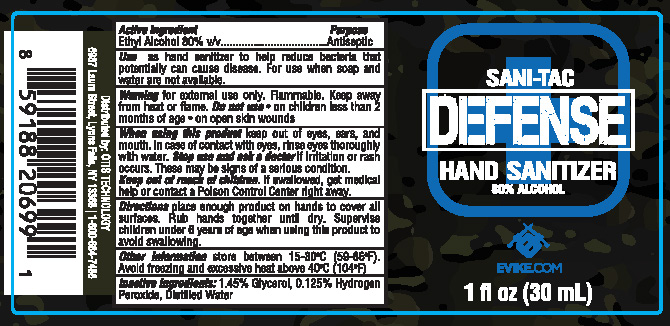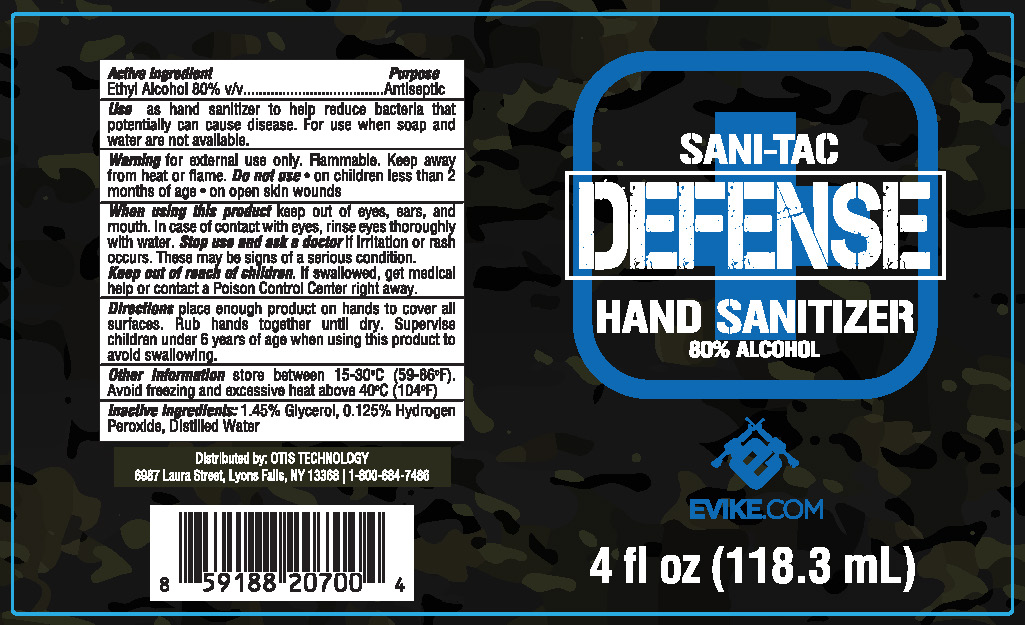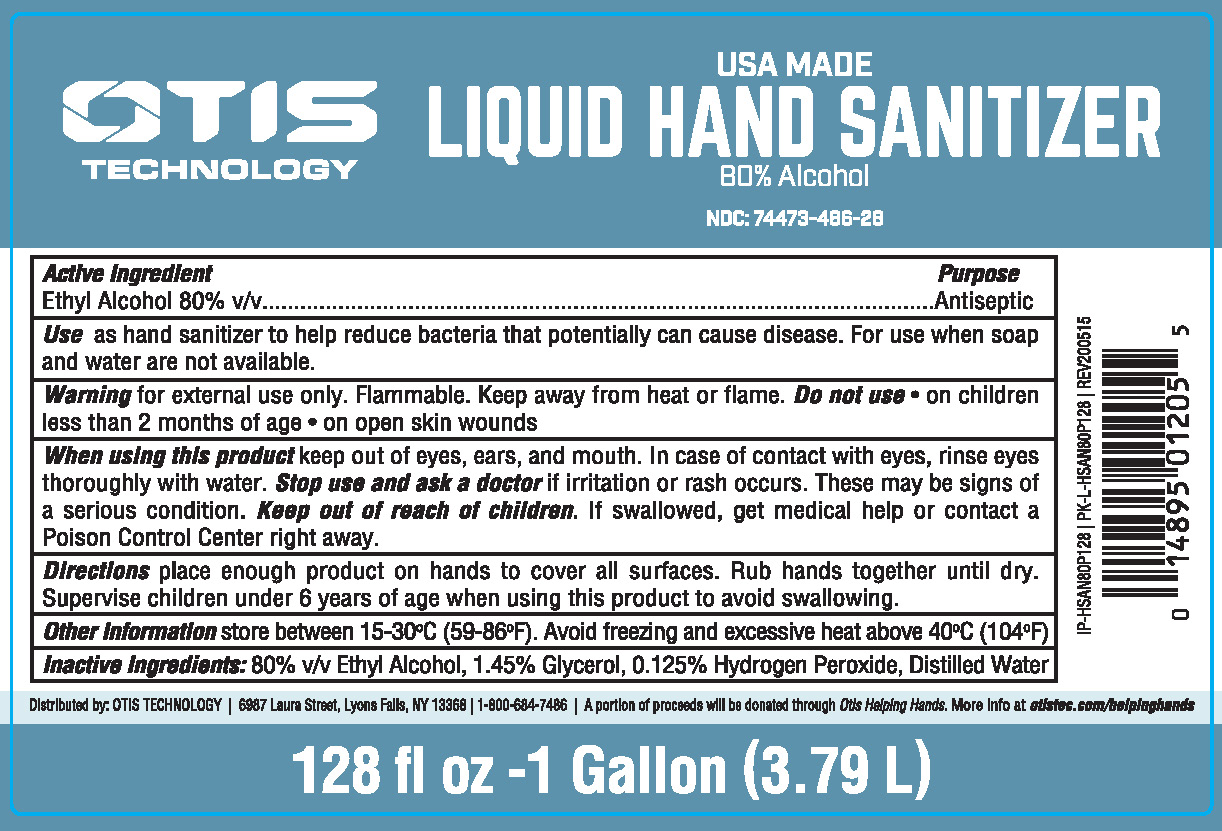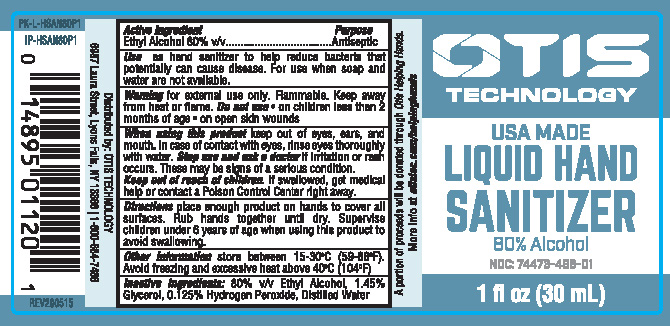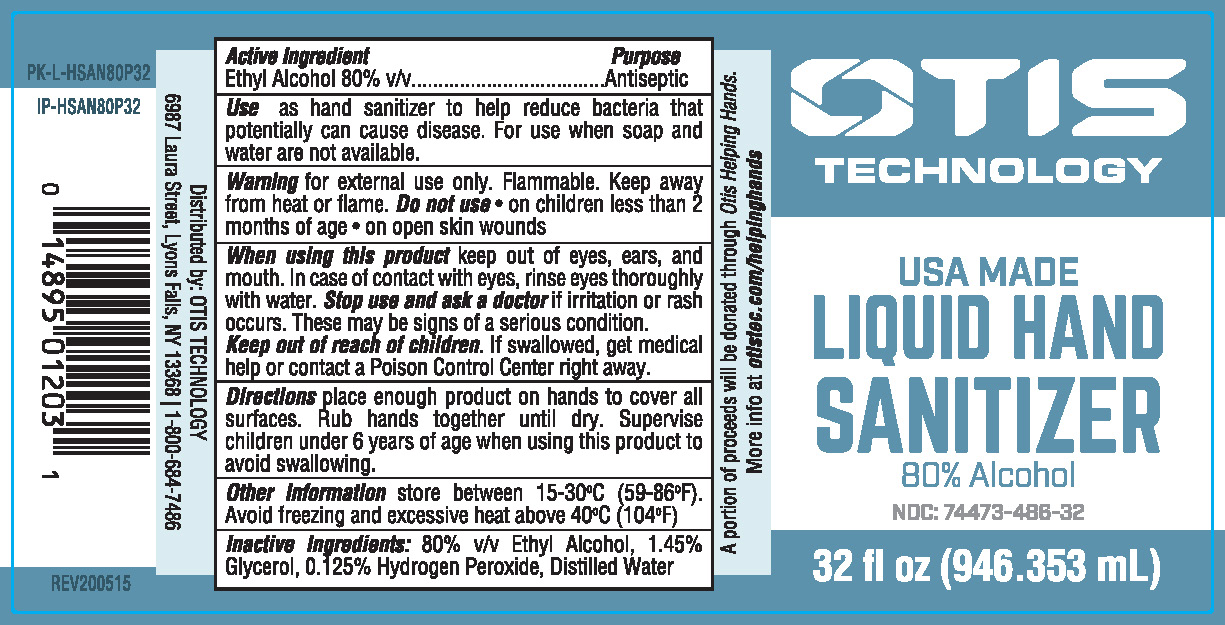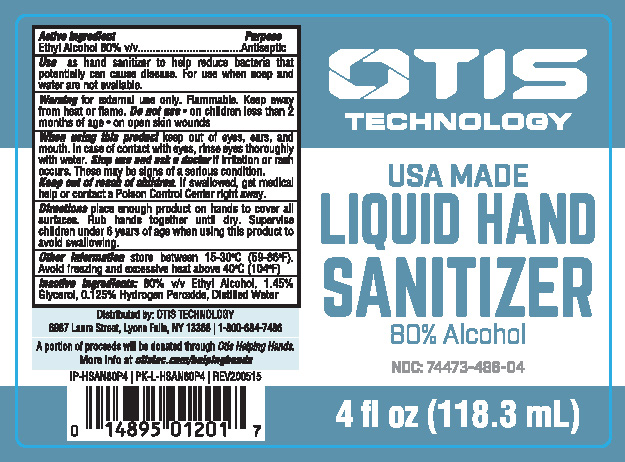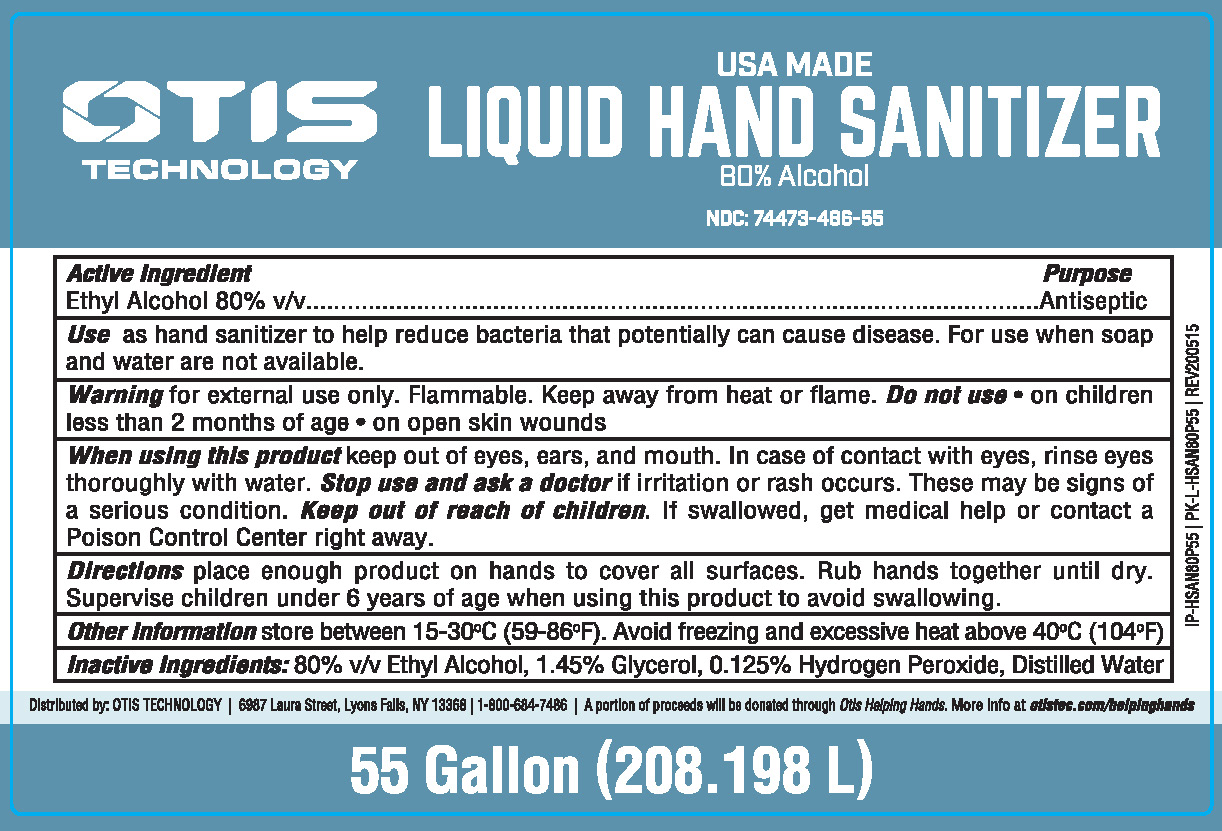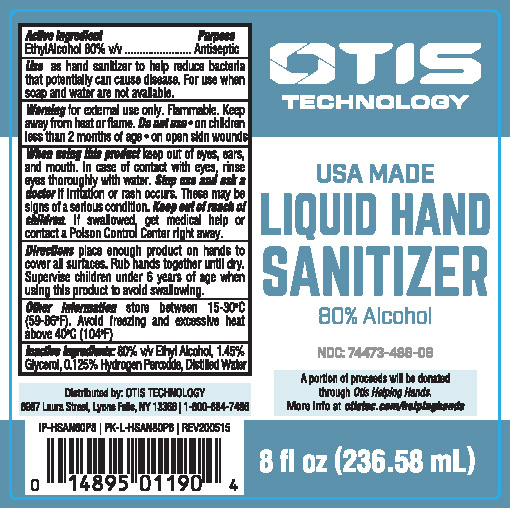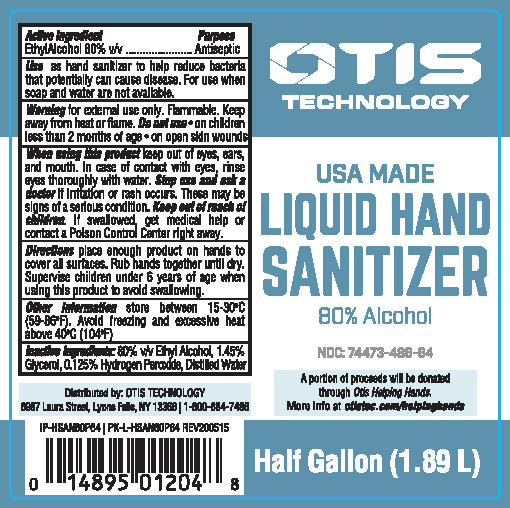 DRUG LABEL: Hand Sanitizer
NDC: 74473-486 | Form: LIQUID
Manufacturer: Otis Products, Inc.
Category: otc | Type: HUMAN OTC DRUG LABEL
Date: 20200602

ACTIVE INGREDIENTS: ALCOHOL 80 mL/100 mL
INACTIVE INGREDIENTS: GLYCERIN 1.45 mL/100 mL; HYDROGEN PEROXIDE 0.125 mL/100 mL; WATER

80% Hand Sanitizer

Active Ingredient(s)

Alcohol 80% v/v. Purpose: Antiseptic

Use

Use as hand sanitizer to help reduce bacteria that potentially can cause disease. For use when soup and water are not available.

Warnings

Warning for external use only. Flammable. Keep away from heat or flame.

Do not use

- in children less than 2 months of age
- on open wounds

When using this product keep out of eyes, ears, and mouth. In case of contact with eyes, rinse eyes thoroughly with water.
Stop use and ask a doctor if irritation or rash occurs. These may be signs of a serious condition.

Keep out of reach of children. If swallowed, get medical help or contact a Poison Control Center right away.

Directions

- Place enough product on hands to cover all surfaces. Rub hands together until dry.
- Supervise children under 6 years of age when using this product to avoid swallowing.

Other information

- Store between 15-30C (59-86F)
- Avoid freezing and excessive heat above 40C (104F)

Inactive ingredients

glycerin, hydrogen peroxide, purified water USP

Use

Use as hand sanitizer to help reduce bacteria that potentially can cause disease. For use when soap and water are not available.

Purpose

Antiseptic

Package Label - Principal Display Panel

30 mL NDC: 74473-486-01

118.3 mL NDC: 74473-486-04

236.58 mL NDC: 74473-486-08

946.35 mL NDC: 74473-486-32

3785.4 mL NDC: 74473-486-28

1892.7 mL NDC: 74473-486-64

208197.64 mL NDC: 74473-486-55

118.3 mL NDC: 74473-486-98

30 mL NDC: 74473-486-99